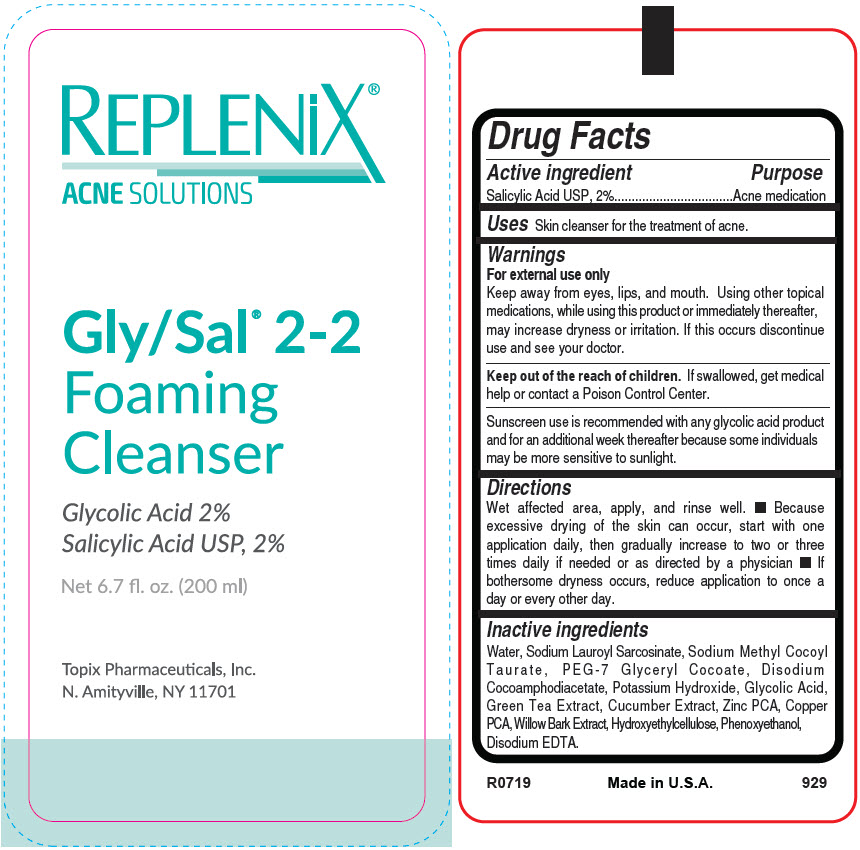 DRUG LABEL: Replenix Acne  Gly-Sal 2-2 Foaming Cleanser
NDC: 51326-929 | Form: LIQUID
Manufacturer: Topiderm, Inc.
Category: otc | Type: HUMAN OTC DRUG LABEL
Date: 20191219

ACTIVE INGREDIENTS: SALICYLIC ACID 20 mg/1 mL
INACTIVE INGREDIENTS: WATER; SODIUM LAUROYL SARCOSINATE; SODIUM METHYL COCOYL TAURATE; PEG-7 GLYCERYL COCOATE; DISODIUM COCOAMPHODIACETATE; POTASSIUM HYDROXIDE; GLYCOLIC ACID; GREEN TEA LEAF; CUCUMBER; ZINC PIDOLATE; COPPER PIDOLATE; WILLOW BARK; HYDROXYETHYL CELLULOSE (100 MPA.S AT 2%); PHENOXYETHANOL; EDETATE DISODIUM ANHYDROUS

Replenix® Acne Solutions Gly-Sal® 2-2 Foaming Cleanser

Drug Facts

Active ingredient

Salicylic Acid USP, 2%

Purpose

Acne medication

Uses

Skin cleanser for the treatment of acne.

Warnings

For external use only

Keep away from eyes, lips, and mouth. Using other topical medications, while using this product or immediately thereafter, may increase dryness or irritation. If this occurs discontinue use and see your doctor.

KEEP OUT OF REACH OF CHILDREN

Keep out of the reach of children. If swallowed, get medical help or contact a Poison Control Center.

Sunscreen use is recommended with any glycolic acid product and for an additional week thereafter because some individuals may be more sensitive to sunlight.

Directions

Wet affected area, apply, and rinse well.

- Because excessive drying of the skin can occur, start with one application daily, then gradually increase to two or three times daily if needed or as directed by a physician
- If bothersome dryness occurs, reduce application to once a day or every other day.

Inactive ingredients

Water, Sodium Lauroyl Sarcosinate, Sodium Methyl Cocoyl Taurate, PEG-7 Glyceryl Cocoate, Disodium Cocoamphodiacetate, Potassium Hydroxide, Glycolic Acid, Green Tea Extract, Cucumber Extract, Zinc PCA, Copper PCA, Willow Bark Extract, Hydroxyethylcellulose, Phenoxyethanol, Disodium EDTA.

PRINCIPAL DISPLAY PANEL - 200 ml Bottle Label

REPLENiX®
ACNE SOLUTIONS

Gly/Sal® 2-2
Foaming
Cleanser

Glycolic Acid 2%
Salicylic Acid USP, 2%

Net 6.7 fl. oz. (200 ml)

Topix Pharmaceuticals, Inc.
N. Amityville, NY 11701